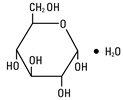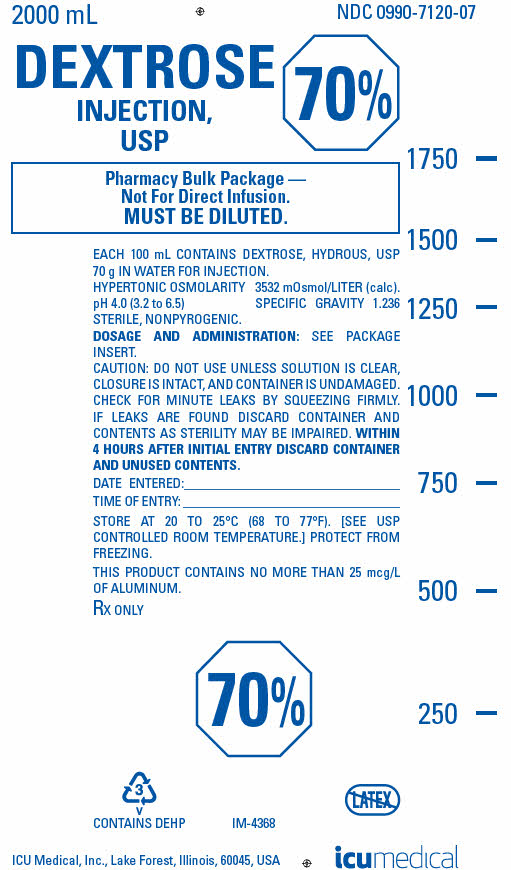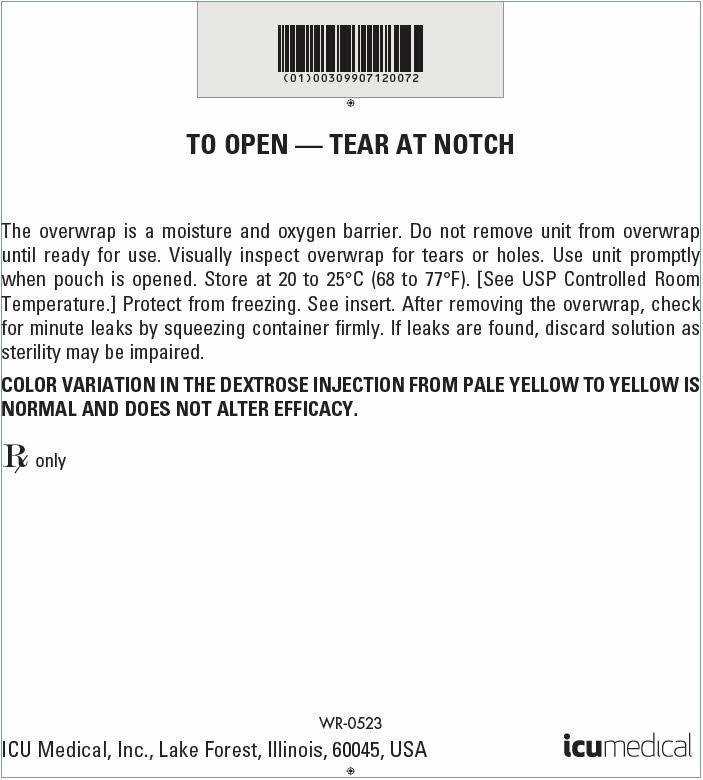 DRUG LABEL: Dextrose
NDC: 0990-7120 | Form: INJECTION, SOLUTION
Manufacturer: ICU Medical Inc.
Category: prescription | Type: HUMAN PRESCRIPTION DRUG LABEL
Date: 20251017

ACTIVE INGREDIENTS: DEXTROSE MONOHYDRATE 70 g/100 mL
INACTIVE INGREDIENTS: WATER

70% Dextrose Injection, USP
Concentrated Dextrose in Water

Pharmacy Bulk Package — Not For Direct Infusion.

FOR USE ONLY WITH AUTOMATED COMPOUNDING DEVICES.

NOTE: These solutions are hypertonic – see WARNINGS and PRECAUTIONS.

Flexible Plastic Containers Rx only

DESCRIPTION

70% Dextrose Injection, USP (concentrated dextrose in water) is a sterile, nonpyrogenic, hypertonic solution of Dextrose, USP in water for injection for intravenous administration after appropriate admixture or dilution.

The Pharmacy Bulk Package is a sterile dosage form which contains multiple single doses for use only in a pharmacy bulk admixture program.

The content and physical characteristics of the solutions are as follows:

Solution; Characteristics | 70% Dextrose; Injection, USP
pH | 4.0
pH range | 3.2 - 6.5
Osmolarity (mOsmol/L) (calc.) | 3532
Specific Gravity | 1.236
Grams Dextrose/100 mL | 70
kcal/100 mL [Caloric value calculated on the basis of 3.4 kcal/g of dextrose, hydrous.] | 238
Fill volume (mL) | 2000

The solutions contain no bacteriostat, antimicrobial agent or added buffer and are intended only for use as a single-dose injection following admixture or dilution.

This Pharmacy Bulk Package is intended only for use in the preparation of sterile, intravenous nutrient admixtures using automated compounding devices. The flexible plastic container is fabricated from a specially formulated polyvinylchloride. Water can permeate from inside the container into the overwrap but not in amounts sufficient to affect the solution significantly. Solutions in contact with the plastic container may leach out certain chemical components from the plastic in very small amounts; however, biological testing was supportive of the safety of the plastic container materials. Exposure to temperatures above 25°C/77°F during transport and storage will lead to minor losses in moisture content. Higher temperatures lead to greater losses. It is unlikely that these minor losses will lead to clinically significant changes within the expiration period.

Dextrose Injection, USP is a parenteral fluid and nutrient replenisher.

Dextrose, USP is chemically designated D-glucose, monohydrate (C6H12O6 • H2O), a hexose sugar freely soluble in water. It has the following structural formula:

Water for Injection, USP is chemically designated H2O.

CLINICAL PHARMACOLOGY

When administered intravenously, solutions containing carbohydrate in the form of dextrose restore blood glucose levels and provide calories. Carbohydrate in the form of dextrose may aid in minimizing liver glycogen depletion and exerts a protein sparing action. Dextrose injection undergoes oxidation to carbon dioxide and water.

Water is an essential constituent of all body tissues and accounts for approximately 70% of total body weight. Average normal adult daily requirement ranges from two to three liters (1.0 to 1.5 liters each for insensible water loss by perspiration and urine production).

Water balance is maintained by various regulatory mechanisms. Water distribution depends primarily on the concentration of electrolytes in the body compartments, and sodium (NA^+) plays a major role in maintaining physiologic equilibrium.

INDICATIONS AND USAGE

70% Dextrose Injection, USP (concentrated dextrose in water) in Pharmacy Bulk Packages is indicated for use with automated compounding devices for preparing intravenous nutritional admixtures in the pharmacy.

CONTRAINDICATIONS

A concentrated dextrose solution should not be used when intracranial or intraspinal hemorrhage is present nor in the presence of delirium tremens if the patient is already dehydrated.

Dextrose injection without electrolytes should not be administered simultaneously with blood through the same infusion set because of the possibility that pseudoagglutination of red cells may occur.

WARNINGS

Concentrated dextrose in water should be administered only after suitable dilution. Hypertonic dextrose solutions should be given slowly. Significant hyperglycemia and possible hyperosmolar syndrome may result from too rapid administration. The physician should be aware of the symptoms of hyperosmolar syndrome, such as mental confusion and loss of consciousness, especially in patients with chronic uremia and those with known carbohydrate intolerance.

The intravenous administration of these solutions can cause fluid and/or solute overloading resulting in dilution of serum electrolyte concentrations, overhydration, congested states or pulmonary edema.

WARNING: This product contains aluminum that may be toxic. Aluminum may reach toxic levels with prolonged parenteral administration if kidney function is impaired. Premature neonates are particularly at risk because their kidneys are immature, and they require large amounts of calcium and phosphate solutions, which contain aluminum.

Research indicates that patients with impaired kidney function, including premature neonates, who receive parenteral levels of aluminum at greater than 4 to 5 mcg/kg/day accumulate aluminum at levels associated with central nervous system and bone toxicity. Tissue loading may occur at even lower rates of administration.

FOR PERIPHERAL VEIN ADMINISTRATION

Hypertonic dextrose solutions (above 5% concentration) should be given slowly, preferably through a small bore needle into a large vein, to minimize venous irritation.

FOR CENTRAL VENOUS ADMINISTRATION

Concentrated dextrose should be administered via central vein after appropriate admixture or dilution when required.

PRECAUTIONS

Electrolyte deficits, particularly in serum potassium and phosphate, may occur during prolonged use of concentrated dextrose solutions. Blood electrolyte monitoring is essential, and fluid and electrolyte imbalances should be corrected. Essential vitamins and minerals also should be provided as needed.

To minimize hyperglycemia and consequent glycosuria, it is desirable to monitor blood and urine glucose and if necessary, add insulin. When concentrated dextrose infusion is abruptly withdrawn, it is advisable to follow with the administration of 5% or 10% dextrose to avoid rebound hypoglycemia.

Aseptic technique is essential with the use of sterile preparations for compounding nutritional admixtures. Discard container within 4 hours of entering closure.

Solutions containing dextrose should be used with caution in patients with known subclinical or overt diabetes mellitus.

Care should be exercised to insure that the needle (or catheter) is well within the lumen of the vein and that extravasation does not occur.

Concentrated dextrose solutions should not be administered subcutaneously or intramuscularly.

Do not administer unless solution is clear and container is undamaged.

Pregnancy Category C: Animal reproduction studies have not been conducted with dextrose. It is also not known whether dextrose can cause fetal harm when administered to a pregnant woman or can affect reproduction capacity. Dextrose should be given to a pregnant woman only if clearly needed.

Pediatric Use

The safety and effectiveness in the pediatric population are based on the similarity of the clinical conditions of the pediatric and adult populations. In neonates or very small infants the volume of fluid may affect fluid and electrolyte balance. Caution should be exercised with low birth weight premature neonates, who are receiving dextrose concentrations of 10% or greater, as they are most susceptible to glucose intolerance and hyperglycemia. Frequent monitoring of serum glucose concentrations is required when dextrose is prescribed to pediatric patients, particularly neonates and low birth weight infants.

In very low birth weight infants, excessive or rapid administration of dextrose injection may result in increased serum osmolality and possible intracerebral hemorrhage.

ADVERSE REACTIONS

Hyperosmolar syndrome, resulting from excessively rapid administration of concentrated dextrose may cause hypovolemia, dehydration, mental confusion and/or loss of consciousness.

Reactions which may occur because of the solution or the technique of administration include febrile response, infection at the site of injection, venous thrombosis or phlebitis extending from the site of injection, extravasation and hypervolemia.

If an adverse reaction does occur, discontinue the infusion, evaluate the patient, institute appropriate therapeutic countermeasures and save the remainder of the fluid for examination if deemed necessary.

OVERDOSAGE

In the event of overhydration or solute overload during therapy, re-evaluate the patient and institute appropriate corrective measures. (See WARNINGS and PRECAUTIONS).

DOSAGE AND ADMINISTRATION

Concentrated Dextrose in Water is administered by slow intravenous infusion (a) after admixture with amino acid solutions or (b) after dilution with other compatible IV fluids. Dosage should be adjusted to meet the requirements of each individual patient.

70% Dextrose Injection, USP in the 2000 mL flexible Pharmacy Bulk Package is designed for use with automated compounding devices for preparing intravenous nutritional admixtures. Dosages will be in accordance with the recommendation of the prescribing physician. 70% Dextrose Injection, USP are not intended for direct infusion. Admixtures should be made by, or under the direction of, a pharmacist using strict aseptic technique under a laminar flow hood. Compounded admixtures may be stored under refrigeration for up to 24 hours. Administration of admixtures should be completed within 24 hours after removal from refrigeration.

The maximum rate at which dextrose can be infused without producing glycosuria is 0.5 g/kg of body weight/hr. About 95% of the dextrose is retained when infused at a rate of 0.8 g/kg/hr.

Clinical evaluation and periodic laboratory determinations are necessary to monitor changes in fluid balance, electrolyte concentrations, and acid base balance during prolonged parenteral therapy or whenever the condition of the patient warrants such evaluation.

As reported in the literature, the dosage and constant infusion rate of intravenous dextrose must be selected with caution in pediatric patients, particularly neonates and low birth weight infants, because of the increased risk of hyperglycemia/hypoglycemia.

Parenteral drug products should be inspected visually for particulate matter and discoloration prior to administration, whenever solution and container permit. (See PRECAUTIONS.)

Drug Interactions

Additives may be incompatible with the fluid withdrawn from this container. Consult with pharmacist, if available. When compounding admixtures, use aseptic technique, mix thoroughly and do not store.

Some opacity of the plastic due to moisture absorption during sterilization process may be observed. This is normal and does not affect the solution quality or safety. The opacity will diminish gradually.

Recommended Directions for Use of the Pharmacy Bulk Package Use Aseptic Technique

1. During use, container must be stored, and all manipulations performed, in an appropriate laminar flow hood.
2. Remove cover from outlet port at bottom of container.
3. Insert piercing pin of transfer set and suspend unit in a laminar flow hood. Insertion of a piercing pin into the outlet port should be performed only once in a Pharmacy Bulk Package solution. Once the outlet site has been entered, the withdrawal of container contents should be completed promptly in one continuous operation. Should this not be possible, a maximum time of 4 hours from transfer set pin or implement insertion is permitted to complete fluid transfer operations; i.e., discard container no later than 4 hours after initial closure puncture.
4. Sequentially dispense aliquots of 70% Dextrose Injection, USP into IV containers using appropriate transfer set. During fluid transfer operations, the Pharmacy Bulk Package should be maintained under the storage conditions recommended in the labeling.

HOW SUPPLIED

70% Dextrose Injection, USP are supplied as follows:

NDC No. | Container | Concentration | Fill
0409-7120-07 | Flexible Pharmacy Bulk Package | 70% | 2000 mL
0990-7120-07

ICU Medical is transitioning NDC codes from the "0409" to a "0990" labeler code. Both NDC codes are expected to be in the market for a period of time.

Store at 20 to 25°C (68 to 77°F). [See USP Controlled Room Temperature.] Protect from freezing.

Revised: June 2018
EN-4656
ICU Medical, Inc., Lake Forest, Illinois, 60045, USA

PRINCIPAL DISPLAY PANEL - 70 g Bag Label

2000 mL
NDC 0990-7120-07

DEXTROSE
INJECTION,
USP
70%

Pharmacy Bulk Package —
Not For Direct Infusion.
MUST BE DILUTED.

EACH 100 mL CONTAINS DEXTROSE, HYDROUS, USP
70 g IN WATER FOR INJECTION.
HYPERTONIC OSMOLARITY 3532 mOsmol/LITER (calc).
pH 4.0 (3.2 to 6.5) SPECIFIC GRAVITY 1.236
STERILE, NONPYROGENIC.

DOSAGE AND ADMINISTRATION: SEE PACKAGE
INSERT.

CAUTION: DO NOT USE UNLESS SOLUTION IS CLEAR,
CLOSURE IS INTACT, AND CONTAINER IS UNDAMAGED.
CHECK FOR MINUTE LEAKS BY SQUEEZING FIRMLY.
IF LEAKS ARE FOUND DISCARD CONTAINER AND
CONTENTS AS STERILITY MAY BE IMPAIRED. WITHIN
4 HOURS AFTER INITIAL ENTRY DISCARD CONTAINER
AND UNUSED CONTENTS.

DATE ENTERED:

TIME OF ENTRY:

STORE AT 20 TO 25°C (68 TO 77°F). [SEE USP
CONTROLLED ROOM TEMPERATURE.] PROTECT FROM
FREEZING.

THIS PRODUCT CONTAINS NO MORE THAN 25 mcg/L
OF ALUMINUM.

RX ONLY

70%

3
V
CONTAINS DEHP

IM-4368

ICU Medical, Inc., Lake Forest, Illinois, 60045, USA
icumedical

PRINCIPAL DISPLAY PANEL - 70 g Bag Overwrap Label

TO OPEN — TEAR AT NOTCH

The overwrap is a moisture and oxygen barrier. Do not remove unit from overwrap
until ready for use. Visually inspect overwrap for tears or holes. Use unit promptly
when pouch is opened. Store at 20 to 25°C (68 to 77°F). [See USP Controlled Room
Temperature.] Protect from freezing. See insert. After removing the overwrap, check
for minute leaks by squeezing container firmly. If leaks are found, discard solution as
sterility may be impaired.

COLOR VARIATION IN THE DEXTROSE INJECTION FROM PALE YELLOW TO YELLOW IS
NORMAL AND DOES NOT ALTER EFFICACY.

Rx only

WR-0523

ICU Medical, Inc., Lake Forest, Illinois, 60045, USA
icumedical